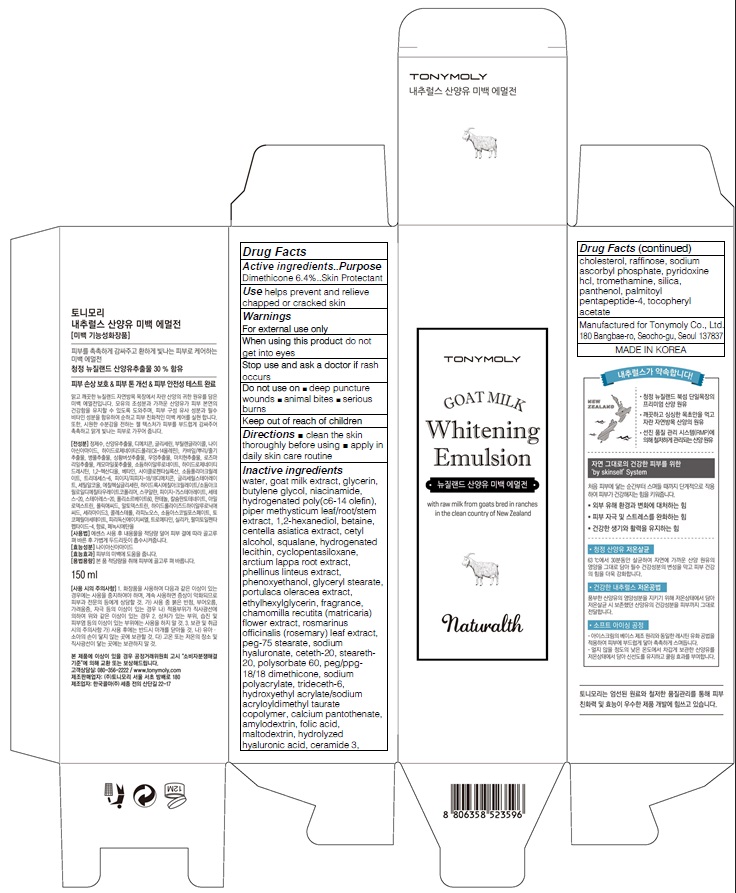 DRUG LABEL: TONYMOLY NATURALTH GOAT MILK WHITENING
NDC: 59078-112 | Form: EMULSION
Manufacturer: TONYMOLY CO.,LTD
Category: otc | Type: HUMAN OTC DRUG LABEL
Date: 20160120

ACTIVE INGREDIENTS: Dimethicone 9.6 g/150 mL
INACTIVE INGREDIENTS: water; goat milk

ACTIVE INGREDIENT

Active ingredients: Dimethicone 6.4%

INACTIVE INGREDIENT

Inactive ingredients water, goat milk extract, glycerin, butylene glycol, niacinamide, hydrogenated poly(c6-14 olefin), piper methysticum leaf/root/stem extract, 1,2-hexanediol, betaine, centella asiatica extract, cetyl alcohol, squalane, hydrogenated lecithin, cyclopentasiloxane, arctium lappa root extract, phellinus linteus extract, phenoxyethanol, glyceryl stearate, portulaca oleracea extract, ethylhexylglycerin, fragrance, chamomilla recutita (matricaria) flower extract, rosmarinus officinalis (rosemary) leaf extract, peg-75 stearate, sodium hyaluronate, ceteth-20, steareth-20, polysorbate 60, peg/ppg-18/18 dimethicone, sodium polyacrylate, trideceth-6, hydroxyethyl acrylate/sodium acryloyldimethyl taurate copolymer, calcium pantothenate, amylodextrin, folic acid, maltodextrin, hydrolyzed hyaluronic acid, ceramide 3, cholesterol, raffinose, sodium ascorbyl phosphate, pyridoxine hcl, tromethamine, silica, panthenol, palmitoyl pentapeptide-4, tocopheryl acetate

PURPOSE

Purpose: Skin Protectant

WARNINGS

Warnings: For external use only

When using this product do not get into eyes

Stop use and ask a doctor if rash occurs

Do not use on - deep puncture wounds - animal bites - serious burns

Keep out of reach of children

KEEP OUT OF REACH OF CHILDREN

Use

Use: helps prevent and relieve chapped or cracked skin

Directions

Directions: - clean the skin thoroughly before using - apply in daily skin care routine